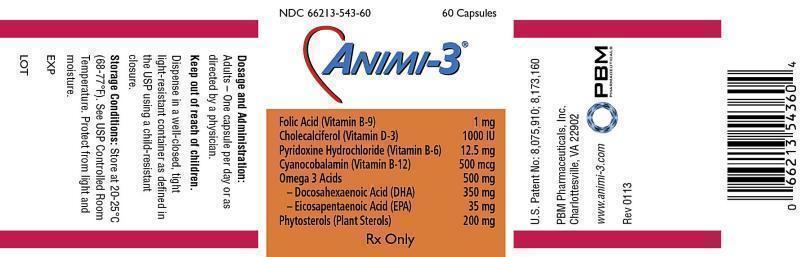 DRUG LABEL: Animi-3
NDC: 66213-543 | Form: CAPSULE
Manufacturer: PBM Pharmaceuticals, Inc
Category: prescription | Type: HUMAN PRESCRIPTION DRUG LABEL
Date: 20130206

ACTIVE INGREDIENTS: Folic Acid 1 mg/1 1; Cholecalciferol 1000 [iU]/1 1; Pyridoxine Hydrochloride 12.5 mg/1 1; Cyanocobalamin 500 ug/1 1; Omega-3 Fatty Acids 500 mg/1 1; Doconexent 250 mg/1 1; Icosapent 35 mg/1 1; Soy Sterol 200 mg/1 1
INACTIVE INGREDIENTS: Ascorbic Acid; Alpha-Tocopherol; Ascorbyl Palmitate; Gelatin; Glycerin; Titanium Dioxide; FD&C Red No. 40; Water; Lecithin, Soybean; FD&C Yellow No. 6

PBM - Animi-3® - Drug Facts

Package Insert

Animi-3®
Each Capsule Contains:
Folic Acid (Vitamin B9) 1mg
Cholecalciferol (Vitamin D3) 1000IU
Pyridoxine Hydrochloride (Vitamin B6) 12.5mg
Cyanocobalamin (Vitamin B12) 500mcg
Omega-3 Acids 500mg
-Docosahexaenoic Acid (DHA) 350mg
-Eicosapentaenoic Acid (EPA) 35mg
Phytosterols (Plant Sterols) 200mg

U.S. Patent No. 8,075,910; 8,173,160
Rx Only

Description

Animi-3® Capsules are intended for oral administration.
Each Capsule Contains: 1mg Vitamin B-9 (Folic Acid USP), 1000IU Vitamin D-3 (Cholecalciferol), 12.5mg Vitamin B-6 (Pyridoxine Hydrochloride, USP), 500mcg vitamin B-12 (Cyanocobalamin, USP), Pharmaceutical Grade omega-3 Fish Oil providing 500mg Omega-3 Acids; including 350mg Docosahexaenoic Acid (DHA) and 35mg Eicosapentaenoic Acid (EPA) and 200mg Plant Sterols (Phytosterols).
Also Contains: Bleached Lecithin NF, Ascorbic Acid USP, Mixed Tocopherols NF, Ascorbyl Palmitate NF and a soft shell capsule (which contains; Gelatin USP, Glycerin NF, Titanium Dioxide USP, FD and C Red #40, FD and C Yellow #6 and USP Purified Water).

Indication

Animi-3® Capsules are indicated for improving nutritional status in conditions requiring Essential Fatty Acids, Vitamin B12, Vitamin B6, Vitamin D3 and Folic Acid supplementation.

CONTRAINDICATIONS

This product is contraindicated in patients with a known hyper-sensitivity to any of the ingredients.

Warning

Ingestion of more than 3 grams of omega-3 fatty acids per day has been shown to have potential antithrombotic effects, including an increased bleeding time and INR. Administration of omega-3 fatty acids should be avoided in patients on anti-coagulants and in those known to have inherited or acquired bleeding diathesis.

Warning

Folic Acid alone is improper therapy in the treatment of pernicious anemia and other megaloblastic anemias where vitamin B12 is deficient. Folic acid in doses above 1.0mg daily may obscure pernicious anemia, in that hematologic remission can occur while neurological manifestations remain progressive.

Pediatric Use

Safety and effectiveness in pediatric patients have not been established.

Pregnancy and Lactation

The safety of phytosterols has not been studied in pregnant or breastfeeding women. There is no evidence that dietary intakes of naturally occurring phytosterols, such as those consumed by vegetarian women, adversely affects pregnancy or lactation.

Adverse Reactions

Allergic sensitization has been reported following oral, enteral and parenteral administration of folic acid.

Dosage and Administration

Adults – One capsule per day or as directed by a physician.

How Supplied

Animi-3® supplied as orange opaque oblong capsules. Each capsule in imprinted with “Animi-3” in black opacode. Animi-3® Capsules are available in bottles of 60 capsules (NDC 66213-543-60).

Keep out of reach of children.

Dispense in a well-closed, tight light-resistant container as defined in the USP using a child-resistant closure.

Storage Conditions:

Store at 20-25°C (68-77°F). See USP Controlled Room Temperature. Protect from light and moisture.

PBM Pharmaceuticals, Inc.
Charlottesville, VA 22902
Rev. 0113
©2013 All Rights Reserved.

PACKAGE LABEL

NDC 66213-543-60 60 Capsules
Animi-3®
Folic Acid (Vitamin B-9) 1 mg
Cholecalciferol (Vitamin D-3) 1000 IU
Pyridoxine Hydrochloride (Vitamin B-6) 12.5 mg
Cyanocobalamin (Vitamin B-12) 500 mcg
Omega 3 Acids 500 mg
– Docosahexaenoic Acid (DHA) 350 mg
– Eicosapentaenoic Acid (EPA) 35 mg
Phytosterols (Plant Sterols) 200 mg
Rx Only